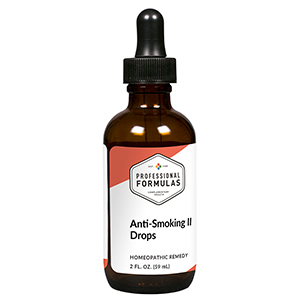 DRUG LABEL: Anti-Smoking II Drops
NDC: 63083-2008 | Form: LIQUID
Manufacturer: Professional Complementary Health Formulas
Category: homeopathic | Type: HUMAN OTC DRUG LABEL
Date: 20190815

ACTIVE INGREDIENTS: SUS SCROFA ADRENAL GLAND 6 [hp_X]/59 mL; BEEF KIDNEY 6 [hp_X]/59 mL; LOBELIA INFLATA WHOLE 6 [hp_X]/59 mL; BEEF LUNG 6 [hp_X]/59 mL; COFFEA ARABICA SEED, ROASTED 6 [hp_X]/59 mL; BETA-ENDORPHIN HUMAN 6 [hp_X]/59 mL; STRYCHNOS NUX-VOMICA SEED 12 [hp_X]/59 mL; SUCROSE 30 [hp_X]/59 mL; NICOTINE 30 [hp_X]/59 mL; TOBACCO LEAF 30 [hp_X]/59 mL
INACTIVE INGREDIENTS: ALCOHOL; WATER

C8

ACTIVE INGREDIENTS

Adrenal 6X
Kidney 6X
Lobelia inflata 6X
Lung 6X
Coffea tosta 6X, 30X, 100X
Endorphins 6X, 30X
Nux vomica 12X, 30X
Saccharum officinale 30X, 60X
Nicotinum 30X, 60X, 100X
Tabacum 30X, 60X, 100X

QUESTIONS

Professional Formulas

PO Box 2034 Lake Oswego, OR 97035

INDICATIONS

For the temporary relief of cravings, occasional headache, cough, irritability, anxiousness, or difficulty concentrating after quitting smoking.*

PURPOSE

*Claims based on traditional homeopathic practice, not accepted medical evidence. Not FDA evaluated.

WARNINGS

In case of overdose, get medical help or contact a poison control center right away.

Keep out of the reach of children.

PREGNANCY OR BREAST FEEDING

If pregnant or breastfeeding, ask a healthcare professional before use.

DIRECTIONS

Place drops under tongue 30 minutes before/after meals. Adults and children 12 years and over: Take 10 drops up to 3 times per day. Consult a physician for use in children under 12 years of age.

OTHER INFORMATION

Tamper resistant. If seal is broken, do not use. After opening, close container tightly and store at room temperature away from heat.

INACTIVE INGREDIENTS

20% ethanol, purified water.

LABEL

Est 1985

Professional Formulas

Complementary Health

Anti-Smoking II Drops

Homeopathic Remedy

2 FL. OZ. (59 mL)